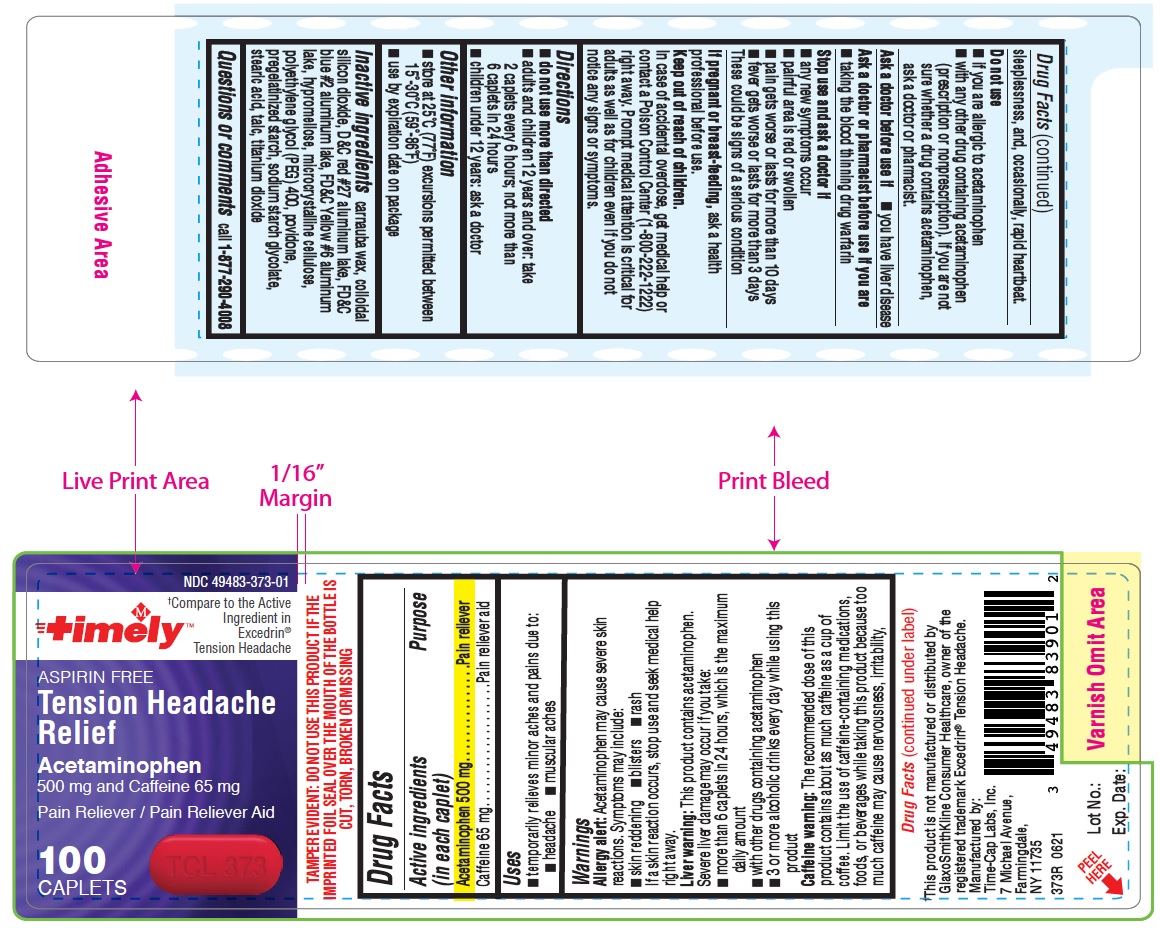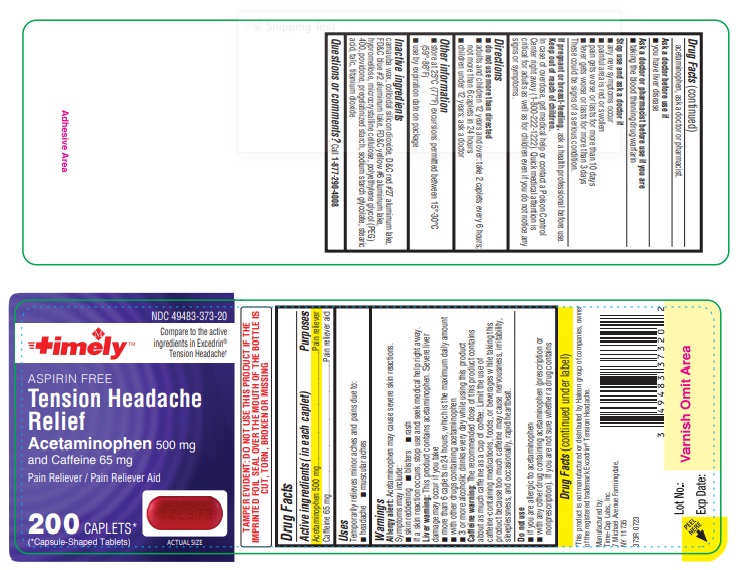 DRUG LABEL: Tension Headache Relief
NDC: 49483-373 | Form: TABLET
Manufacturer: TIME CAP LABS INC
Category: otc | Type: HUMAN OTC DRUG LABEL
Date: 20251021

ACTIVE INGREDIENTS: ACETAMINOPHEN 500 mg/1 1; CAFFEINE 65 mg/1 1
INACTIVE INGREDIENTS: D&C RED NO. 27 ALUMINUM LAKE; FD&C YELLOW NO. 6 ALUMINUM LAKE; POVIDONE; FD&C BLUE NO. 2 ALUMINUM LAKE; STARCH, CORN; CARNAUBA WAX; TALC; POLYETHYLENE GLYCOL, UNSPECIFIED; STEARIC ACID; HYPROMELLOSE, UNSPECIFIED; SILICON DIOXIDE; SODIUM STARCH GLYCOLATE TYPE A CORN; MICROCRYSTALLINE CELLULOSE; TITANIUM DIOXIDE

Timely Tension Headache Relief

Active ingredients (in each caplet)

Acetaminophen 500 mg

Caffeine 65 mg

Purposes

Pain reliever

Pain reliever aid

Uses

Temporarily relieves minor aches and pains due to:

- headache
- muscular aches

Warnings

Allergy alert: Acetaminophen may cause severe skin reactions. Symptoms may include:

- skin reddening
- blisters
- rash

If a skin reaction occurs, stop use and seek medical help right away.

Liver warning: This product contains acetaminophen. Severe liver damage may occur if you take

- more than 6 caplets in 24 hours, which is the maximum daily amount
- with other drugs containing acetaminophen
- 3 or more alcoholic drinks every day while using this product

Caffeine warning: The recommended dose of this product contains about as much caffeine as a cup of coffee. Limit the use of caffeine-containing medications, foods, or beverages while taking this product because too much caffeine may cause nervousness, irritability, sleeplessness, and occasionally, rapid heartbeat.

Do not use

- if you are allergic to acetaminophen
- with any other drug containing acetaminophen (prescription or nonprescription). If you are not sure whether a drug contains acetaminophen, ask a doctor or pharmacist

Ask a doctor before use if

- you have liver disease

Ask a doctor or pharmacist before use if you are

- taking the blood thinning drug warfarin

Stop use and ask a doctor if

- any new symptoms occur
- painful area is red or swollen
- pain gets worse or lasts for more than 10 days
- fever gets worse or lasts for more than 3 days

These could be signs of a serious condition.

PREGNANCY OR BREAST FEEDING

If pregnant or breast-feeding, ask a health professional before use.

Keep out of reach of children.

In case of overdose, get medical help or contact a Poison Control Center right away (1-800-222-1222). Quick medical attention is critical for adults as well as for children even if you do not notice any signs or symptoms.

Directions

- do not use more than directed
- adults and children 12 years and over: take 2 caplets every 6 hours; not more than 6 caplets in 24 hours
- children under 12 years: ask a doctor

Other information

- store at 25°C (77°F) excursions permitted between 15°-30°C (59°-86°F)
- use by expiration date on package

INACTIVE INGREDIENT

Inactive ingredients carnauba wax, colloidal silicon dioxide, D&C red #27 aluminum lake, FD&C blue #2 aluminum lake, FD&C yellow #6 aluminum lake, hypromellose, microcrystalline cellulose, polyethylene glycol (PEG) 400, povidone, pregelatinized starch, sodium starch glycolate, stearic acid, talc, titanium dioxide

Questions or comments? Call 1-877-290-4008